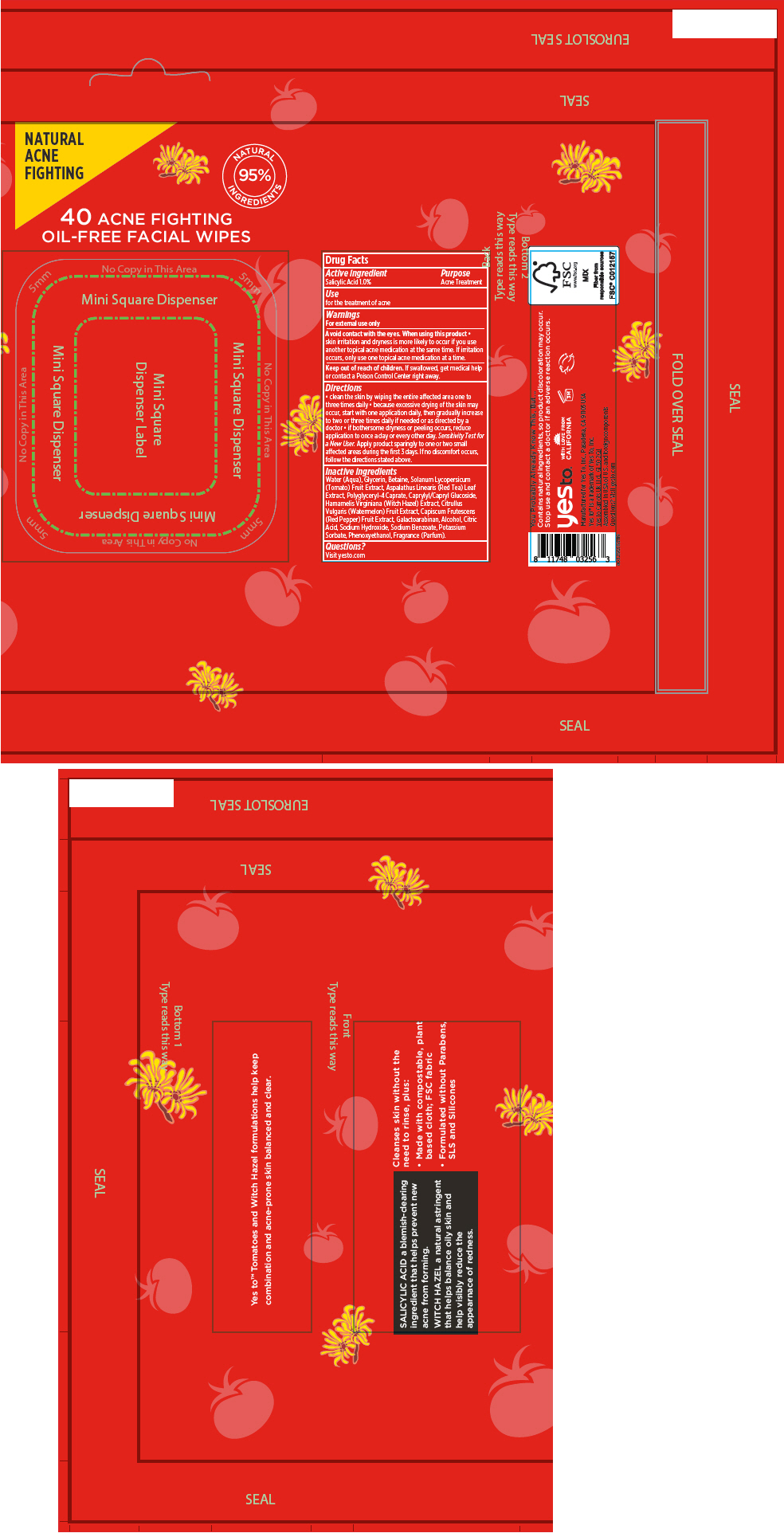 DRUG LABEL: Acne Fighting Oil-Free Facial Wipes
NDC: 69840-016 | Form: CLOTH
Manufacturer: Yes To Inc.
Category: otc | Type: HUMAN OTC DRUG LABEL
Date: 20190422

ACTIVE INGREDIENTS: Salicylic Acid 10 mg/1 1
INACTIVE INGREDIENTS: WATER; GLYCERIN; BETAINE; CAPRYLYL/CAPRYL OLIGOGLUCOSIDE; SOLANUM LYCOPERSICUM; WATERMELON; HAMAMELIS VIRGINIANA TOP; TABASCO PEPPER; ASPALATHUS LINEARIS LEAF; GALACTOARABINAN; ALCOHOL; SODIUM BENZOATE; POTASSIUM SORBATE; PHENOXYETHANOL; SODIUM HYDROXIDE

Acne Fighting Oil-Free Facial Wipes

Drug Facts

Active ingredient

Salicylic Acid 1.0%

Purpose

Acne Treatment

Use

for the treatment of acne

Warnings

For external use only

WHEN USING

Avoid contact with the eyes. When using this product

- skin irritation and dryness is more likely to occur if you use another topical acne medication at the same time. If irritation occurs, only use one topical acne medication at a time.

Keep out of reach of children. If swallowed, get medical help or contact a Poison Control Center right away.

Directions

- clean the skin by wiping the entire affected area one to three times daily
- because excessive drying of the skin may occur, start with one application daily, then gradually increase to two or three times daily if needed or as directed by a doctor
- if bothersome dryness or peeling occurs, reduce application to once a day or every other day.

Sensitivity Test for a New User. Apply product sparingly to one or two small affected areas during the first 3 days. If no discomfort occurs, follow the directions stated above.

Inactive ingredients

Water (Aqua), Glycerin, Betaine, Solanum Lycopersicum (Tomato) Fruit Extract, Aspalathus Linearis (Red Tea) Leaf Extract, Polyglyceryl-4 Caprate, Caprylyl/Capryl Glucoside, Hamamelis Virginiana (Witch Hazel) Extract, Citrullus Vulgaris (Watermelon) Fruit Extract, Capiscum Frutescens (Red Pepper) Fruit Extract, Galactoarabinan, Alcohol, Citric Acid, Sodium Hydroxide, Sodium Benzoate, Potassium Sorbate, Phenoxyethanol, Fragrance (Parfum).

Questions?

Visit yesto.com

PRINCIPAL DISPLAY PANEL - 40 Facial Wipe Packet

NATURAL
ACNE
FIGHTING

NATURAL
95%
INGREDIENTS

40 ACNE FIGHTING
OIL-FREE FACIAL WIPES